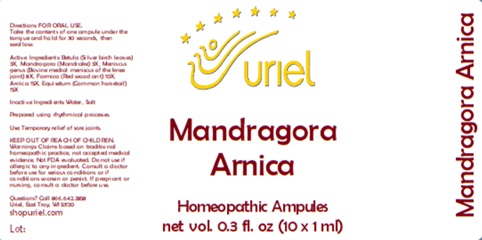 DRUG LABEL: Mandragora Arnica
NDC: 48951-7200 | Form: LIQUID
Manufacturer: Uriel Pharmacy, Inc.
Category: homeopathic | Type: HUMAN OTC DRUG LABEL
Date: 20241113

ACTIVE INGREDIENTS: ARNICA MONTANA WHOLE 15 [hp_X]/1 mL; BETULA PUBESCENS LEAF 3 [hp_X]/1 mL; MANDRAGORA OFFICINARUM ROOT 3 [hp_X]/1 mL; EQUISETUM ARVENSE TOP 15 [hp_X]/1 mL; FORMICA RUFA 10 [hp_X]/1 mL; SUS SCROFA MENISCUS 8 [hp_X]/1 mL
INACTIVE INGREDIENTS: WATER; SODIUM CHLORIDE

Mandragora Arnica

INDICATIONS AND USAGE

Directions: FOR ORAL USE.

DOSAGE AND ADMINISTRATION

Take the contents of one ampule under the tongue and hold for 30 seconds, then swallow.

ACTIVE INGREDIENT

Active Ingredients: Betula (Silver birch leaves) 3X, Mandragora (Mandrake) 3X, Meniscus genus (Bovine medial meniscus of the knee joint) 8X, Formica (Red wood ant) 10X, Arnica 15X, Equisetum (Common horsetail) 15X

Inactive Ingredients: Water, Salt

Prepared using rhythmical processes.

PURPOSE

Use: Temporary relief of sore joints.

KEEP OUT OF REACH OF CHILDREN.

WARNINGS

Warnings: Claims based on traditional homeopathic practice, not accepted medical evidence. Not FDA evaluated. Do not use if allergic to any ingredient. Consult a doctor before use for serious conditions or if conditions worsen or persist. If pregnant or nursing, consult a doctor before use.

Questions? Call 866.642.2858
Uriel, East Troy, WI 53120
www.shopuriel.com Lot: